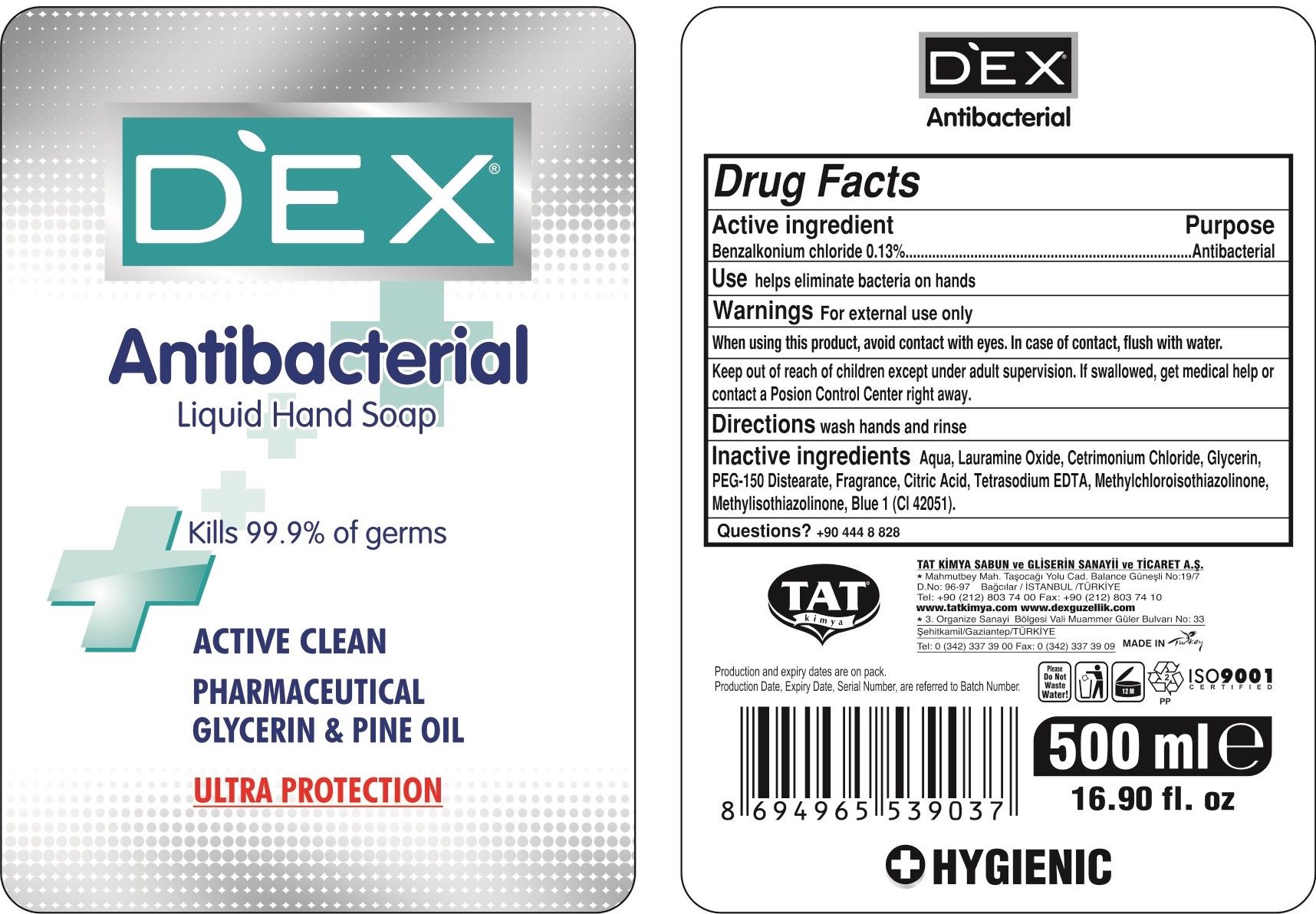 DRUG LABEL: Dex
NDC: 76964-300 | Form: LIQUID
Manufacturer: TAT KIMYA SABUN VE GLISERIN SANAYI VE TICARET ANONIM SIRKETI
Category: otc | Type: HUMAN OTC DRUG LABEL
Date: 20221210

ACTIVE INGREDIENTS: BENZALKONIUM CHLORIDE 0.13 g/100 g
INACTIVE INGREDIENTS: LAURAMINE OXIDE 8 g/100 g; CETRIMONIUM CHLORIDE 3 g/100 g; FRAGRANCE LEMON ORC2001060 0.4 g/100 g; GLYCERIN 2 g/100 g; WATER 84.37 g/100 g; PEG-120 METHYL GLUCOSE DIOLEATE 2 g/100 g; METHYLCHLOROISOTHIAZOLINONE/METHYLISOTHIAZOLINONE MIXTURE 0.1 g/100 g

Active Ingredient(s)

Benzalkonium Chloride %0.13....Purpose: Antibacterial

Purpose

Antibacterial, Liquid Soap

Use

It helps eliminate bacteria on hands.

Warnings

For external use only. When using this product, avoid contact with eyes. In case of contact, flush with water.

Do not use

If swallowed, get medical help or contact a Poison Control Center right away.

When using this product, avoid contact with eyes. Keep out of reach of children. If swallowed, get medical help or contact a Poison Control Center right away.

STOP USE

If swallowed, get medical help or contact a Poison Control Center right away.

Keep out of reach of children. If swallowed, get medical help or contact a Poison Control Center right away.

Directions

- wash hands and rinse

Other information

- Store between 15-30C (59-86F)
- Avoid freezing and excessive heat above 40C (104F)

Inactive ingredients

Aqua, Lauramine Oxide, Cetrimonium Chloride, Glycerin, PEG - 150 Distearate, Fragrance, Citric Acid, Tetrasodium EDTA, Methylchloroisothiazolinone, Methylisothiazolinone, Blue 1(CI 42051)